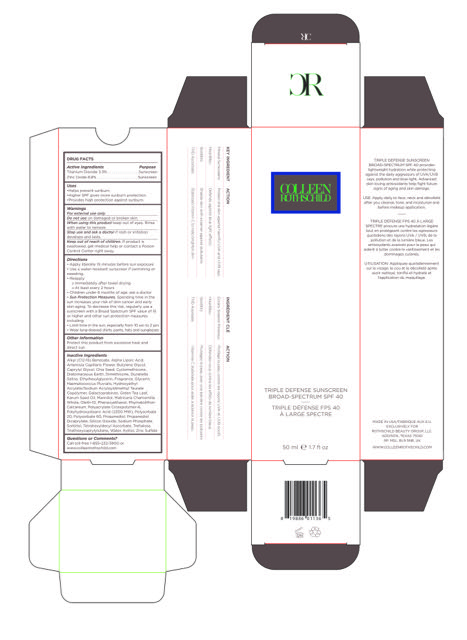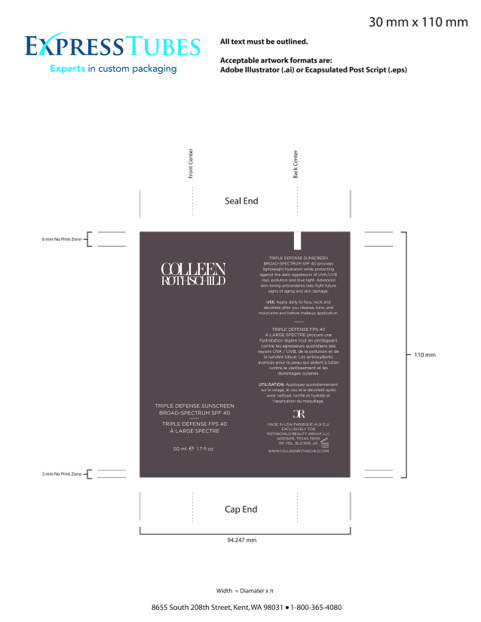 DRUG LABEL: Triple Defense Sunscreen Broad Spectrum SPF 40
NDC: 73040-001 | Form: LOTION
Manufacturer: Rothschild Beauty Group LLC
Category: otc | Type: HUMAN OTC DRUG LABEL
Date: 20201113

ACTIVE INGREDIENTS: ZINC OXIDE 88 mg/1 mL; TITANIUM DIOXIDE 33 mg/1 mL
INACTIVE INGREDIENTS: HAEMATOCOCCUS PLUVIALIS; ZINC SULFATE; TREHALOSE; WATER; XYLITOL; KARUM SEED OIL; ALKYL (C12-15) BENZOATE; DIMETHICONE; GLYCERIN; HYDROXYETHYL ACRYLATE/SODIUM ACRYLOYLDIMETHYL TAURATE COPOLYMER (45000 MPA.S AT 1%); GALACTOARABINAN; PROPANEDIOL; PROPANEDIOL DICAPRYLATE; SILICON DIOXIDE; MANNITOL; MATRICARIA CHAMOMILLA WHOLE; POLYSORBATE 20; POLYSORBATE 60; OLETH-10; SODIUM PHOSPHATE; SORBITOL; TETRAHEXYLDECYL ASCORBATE; TRIETHOXYCAPRYLYLSILANE; ARTEMISIA CAPILLARIS FLOWER; CYCLOMETHICONE; DIATOMACEOUS EARTH; CAPRYLYL GLYCOL; ALPHA LIPOIC ACID; CHIA SEED; DUNALIELLA SALINA; ETHYLHEXYLGLYCERIN; BUTYLENE GLYCOL; GREEN TEA LEAF; AMMONIUM ACRYLOYLDIMETHYLTAURATE, DIMETHYLACRYLAMIDE, LAURYL METHACRYLATE AND LAURETH-4 METHACRYLATE COPOLYMER, TRIMETHYLOLPROPANE TRIACRYLATE CROSSLINKED (45000 MPA.S); POLYHYDROXYSTEARIC ACID (2300 MW); PHENOXYETHANOL; PHYMATOLITHON CALCAREUM

Rothschild Sunscreen SPF40

Active Ingredients

Titanium Dioxide 3.3%

Zinc Oxide 8.8%

Purpose

Sunscreen

Uses

- Helps prevent sunburn
- Higher SPF gives more sunburn protection
- Provides high protection against sunburn

Warnings

For external use only

Do not use

on damaged or broken skin

When using this product

keep out of eyes. Rinse with water to remove.

Stop use and ask a doctor

if rash or irritation develops and lasts.

Keep out of reach of children

If product is swallowed, get medical help or contact a Poison Control Center right away.

Directions

Apply liberally 15 minutes before sun exposure

• Use a water-resistant sunscreen if swimming or sweating.

• Reapply

o Immediately after towel drying

o At least every 2 hours

• Children under 6 months of age: ask a doctor

• Sun Protection Measures. Spending time in the sun increases your risk of skin

cancer and early skin aging. To decrease this risk, regularly use a sunscreen

with a Broad Spectrum SPF value of 15 or higher and other sun protection

measures including:

• limit time in the sun, especially from 10 am to 2 pm

• wear long-sleeved shirts, pants, hats and sunglasses

Other Information

Protect this product from excessive heat and direct sun

Inactive Ingredients

Alkyl (C12-15) Benzoate, Alpha Lipoic Acid, Artemisia Capillaris Flower, Butylene Glycol, Caprylyl Glycol, Chia Seed, Cyclomethicone, Diatomaceous Earth, Dimethicone, Dunaliella Salina, Ethylhexylglycerin, Fragrance, Glycerin, Haematococcus Pluvialis, Hydroxyethyl Acrylate/Sodium Acryloyldimethyl Taurate Copolymer, Galactoarabinan, Green Tea Leaf, Karum Seed Oil, Mannitol, Matricaria Chamomilla Whole, Oleth-10, Phenoxyethanol, Phymatolithon Calcareum, Polyacrylate Crosspolymer-6, Polyhydroxystearic Acid (2300 MW), Polysorbate 20, Polysorbate 60, Propanediol, Propanediol Dicaprylate, Silicon Dioxide, Sodium Phosphate, Sorbitol, Tetrahexyldecyl Ascorbate, Trehalose, Triethoxycaprylylsilane, Water, Xylitol, Zinc Sulfate